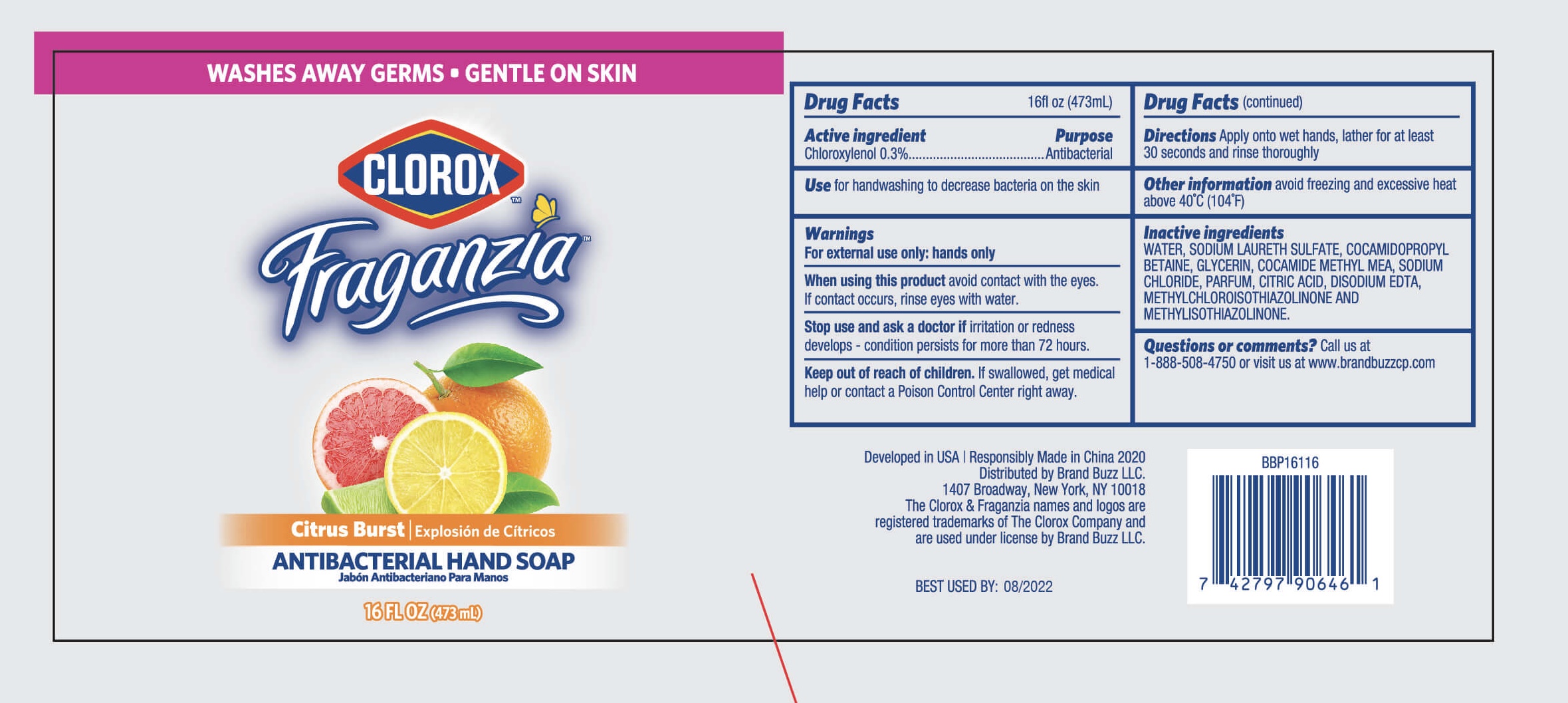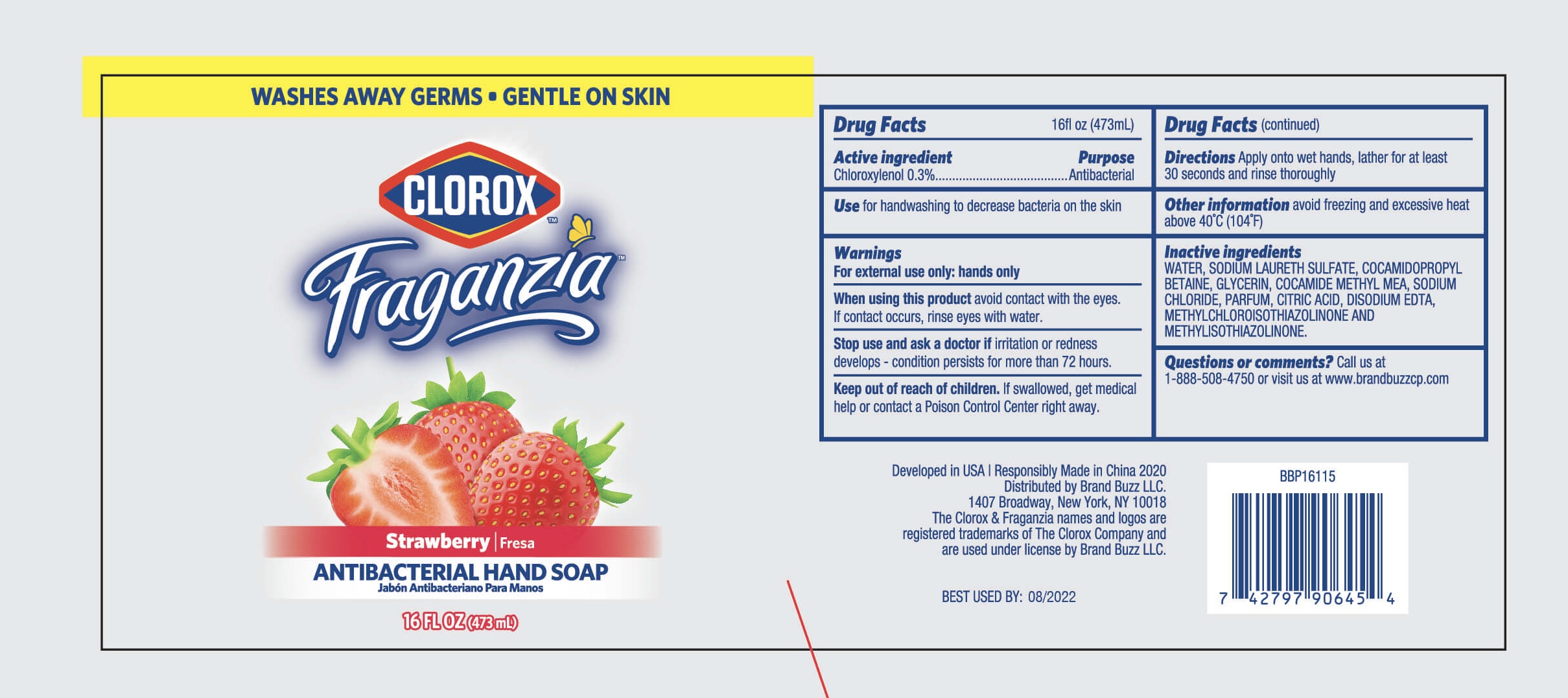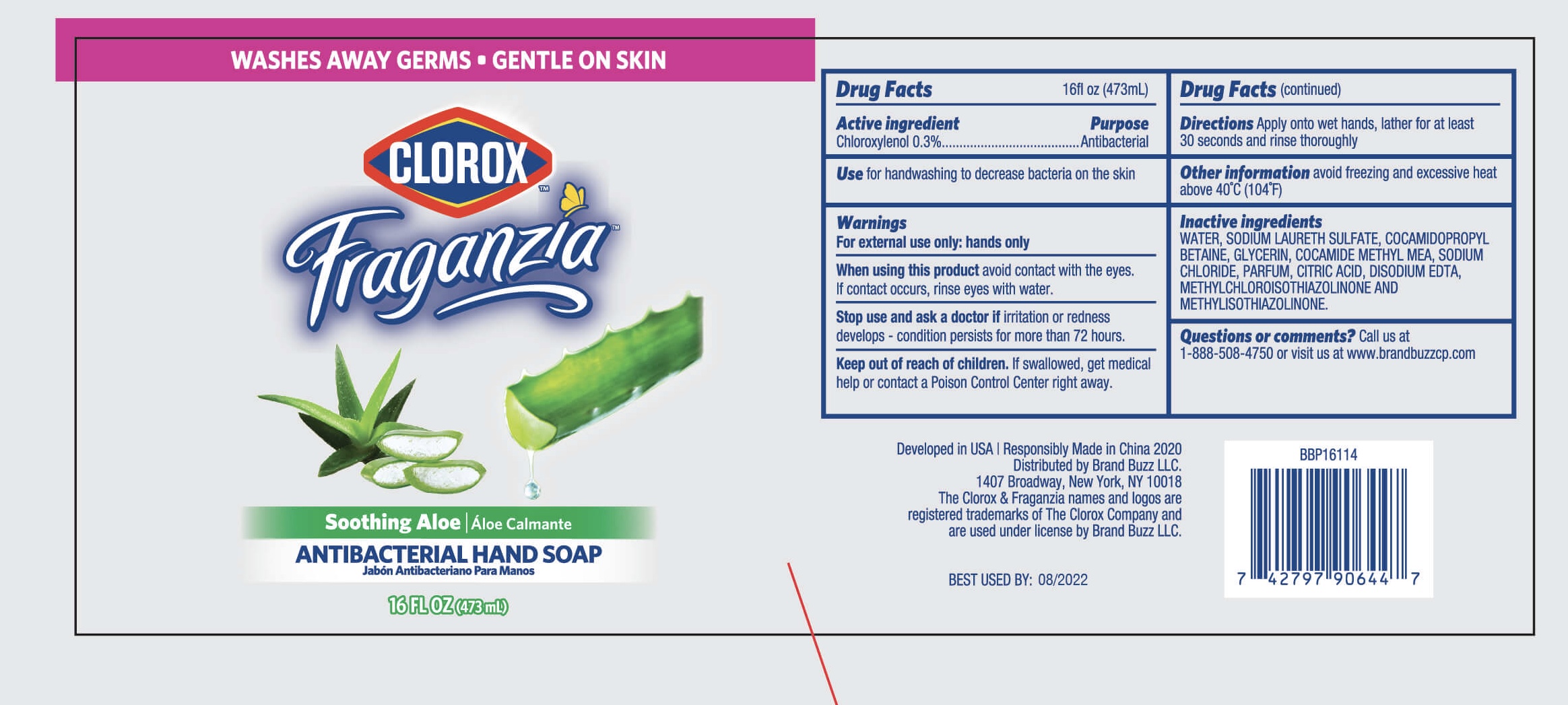 DRUG LABEL: Clorox Fraganzia Antibacterial Hand
NDC: 77720-010 | Form: SOAP
Manufacturer: Skaffles Group Limited Liability Company
Category: otc | Type: HUMAN OTC DRUG LABEL
Date: 20200922

ACTIVE INGREDIENTS: CHLOROXYLENOL 0.3 g/100 mL
INACTIVE INGREDIENTS: WATER; SODIUM LAURETH SULFATE; COCAMIDOPROPYL BETAINE; GLYCERIN; COCOYL METHYL MONOETHANOLAMINE; CITRIC ACID MONOHYDRATE; EDETATE DISODIUM ANHYDROUS; METHYLCHLOROISOTHIAZOLINONE/METHYLISOTHIAZOLINONE MIXTURE; SODIUM CHLORIDE

77720-010 Clorox Fraganzia antibacterial hand soap 0.3%CHLOROXYLENOL

Active Ingredient

Chloroxylenol 0.3%.

Purpose

Antibacterial

USE

For handwashing to decrease bacteria on the skin.

Warning

For external use only: hands only
When using this product avoid contact with the eyes.
If contact occurs, rinse eyes with water.
Stop use and ask a doctor if irritation or redness
develops- condition persists for more than 72 hours.

Keep out of reach of children. If swallowed, get medical help or contact a Poison Control Center right away.

Directions

Directions Apply onto wet hands, lather for at least
30 seconds and rinse thoroughly

Inactive ingredients

WATER,SODIUM LAURETH SULFATE,COCAMIDOPROPYL
BETAINE,GLYCERIN,COCAMIDE METHYL MEA,SODIUM
CHLORIDE,PARFUM,CITRIC ACID,DISODIUM EDTA,
METHYLCHLOROISOTHIAZOLINONE AND
METHYLISOTHIAZOLINONE.